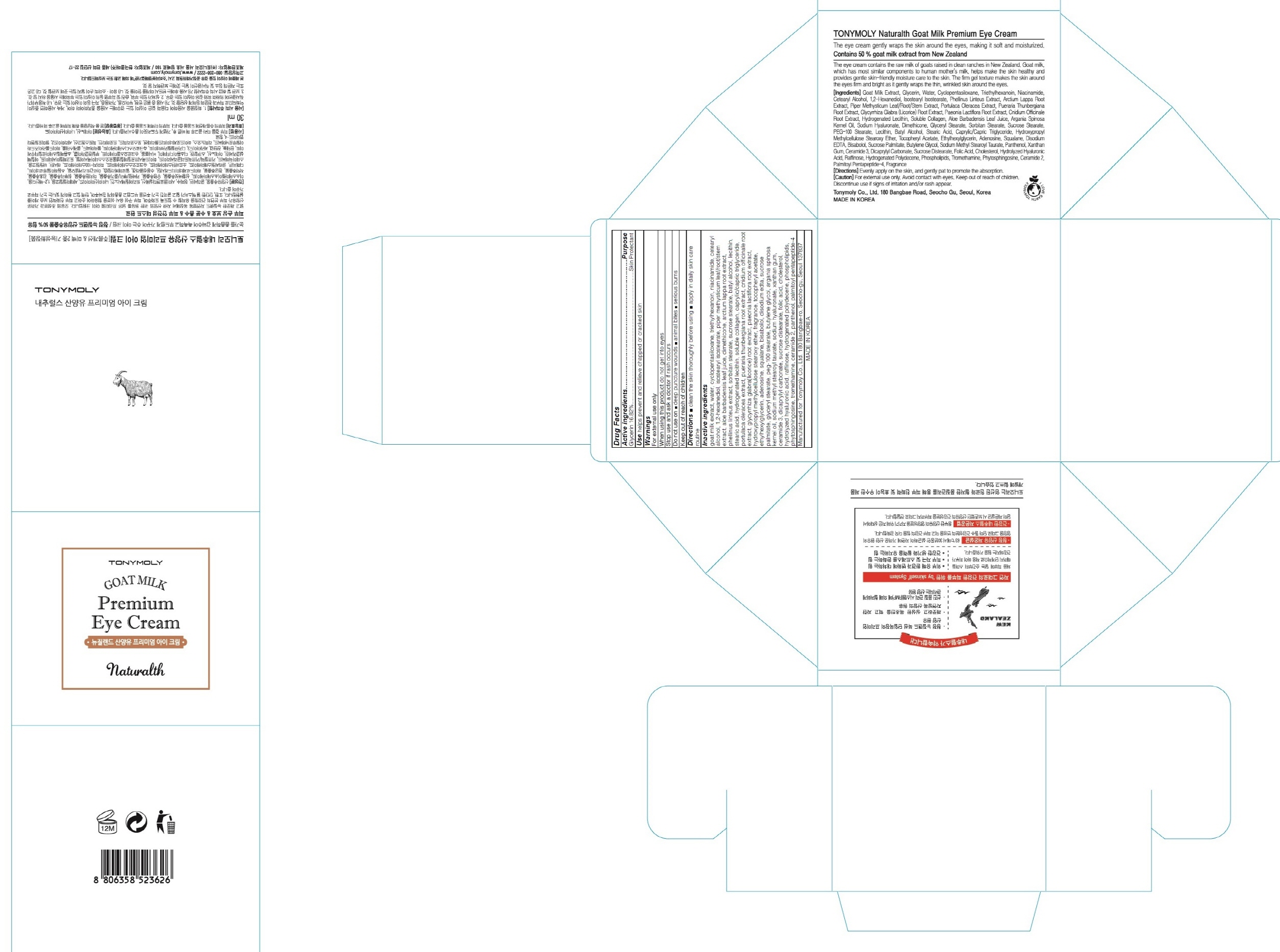 DRUG LABEL: TONYMOLY NATURALTH GOAT MILK PREMIUM EYE
NDC: 59078-240 | Form: CREAM
Manufacturer: TONYMOLY CO.,LTD
Category: otc | Type: HUMAN OTC DRUG LABEL
Date: 20160120

ACTIVE INGREDIENTS: Glycerin 5.04 g/30 mL
INACTIVE INGREDIENTS: goat milk; water

ACTIVE INGREDIENT

Active ingredients: Glycerin 16.82%

INACTIVE INGREDIENT

Inactive ingredients: goat milk extract, water, cyclopentasiloxane, triethylhexanoin, niacinamide, cetearyl alcohol, 1,2-hexanediol, isostearyl isostearate, piper methysticum leaf/root/stem extract, aloe barbadensis leaf juice, dimethicone, arctium lappa root extract, phellinus linteus extract, sorbitan stearate, sucrose stearate, batyl alcohol, lecithin, stearic acid, hydrogenated lecithin, soluble collagen, caprylic/capric triglyceride, portulaca oleracea extract, pueraria thunbergiana root extract, cnidium officinale root extract, glycyrrhiza glabra(licorice) root extract, paeonia lactiflora root extract, hydroxypropyl methylcellulose stearoxy ether, fragrance, tocopheryl acetate, ethylhexylglycerin, adenosine, squalane, bisabolol, disodium edta, sucrose palmitate, glyceryl stearate, peg-100 stearate, butylene glycol, argania spinosa kernel oil, sodium methyl stearoyl taurate, sodium hyaluronate, xanthan gum, ceramide 3, dicaprylyl carbonate, sucrose distearate, folic acid, cholesterol, hydrolyzed hyaluronic acid, raffinose, hydrogenated polydecene, phospholipids, phytosphingosine, tromethamine, ceramide 2, panthenol, palmitoyl pentapeptide-4

PURPOSE

Purpose: Skin Protectant

WARNINGS

Warnings: For external use only

When using this product do not get into eyes

Stop use and ask a doctor if rash occurs

Do not use on - deep puncture wounds - animal bites - serious burns

Keep out of reach of children

KEEP OUT OF REACH OF CHILDREN

Use

Use: helps prevent and relieve chapped or cracked skin

Directions

Directions: - clean the skin thoroughly before using - apply in daily skin care routined